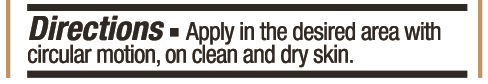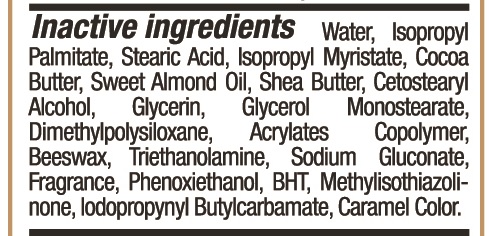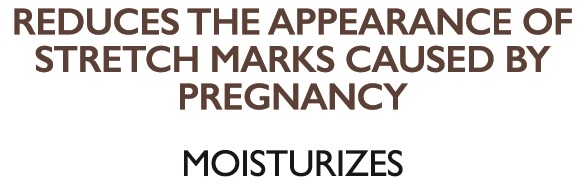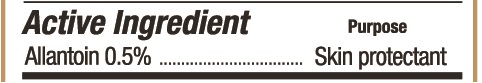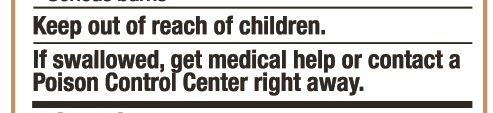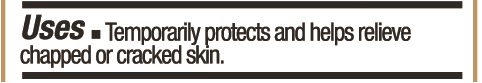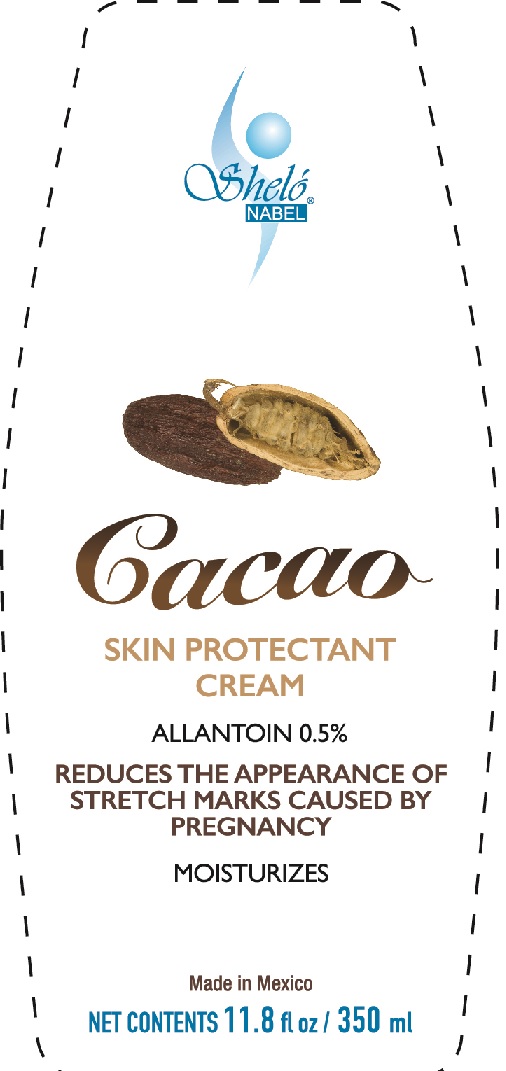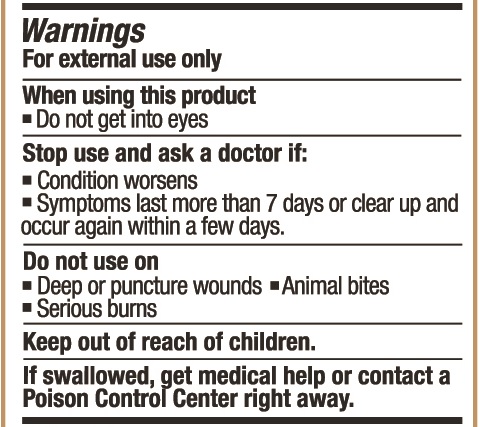 DRUG LABEL: Shelo NABEL CACAO Skin Protectan
NDC: 71424-1146 | Form: CREAM
Manufacturer: Corporativo Serysi S de R L de C V
Category: otc | Type: HUMAN OTC DRUG LABEL
Date: 20191015

ACTIVE INGREDIENTS: ALLANTOIN 5 mg/1 g
INACTIVE INGREDIENTS: ISOPROPYL PALMITATE

CACAO Skin Protectan Cream U0146